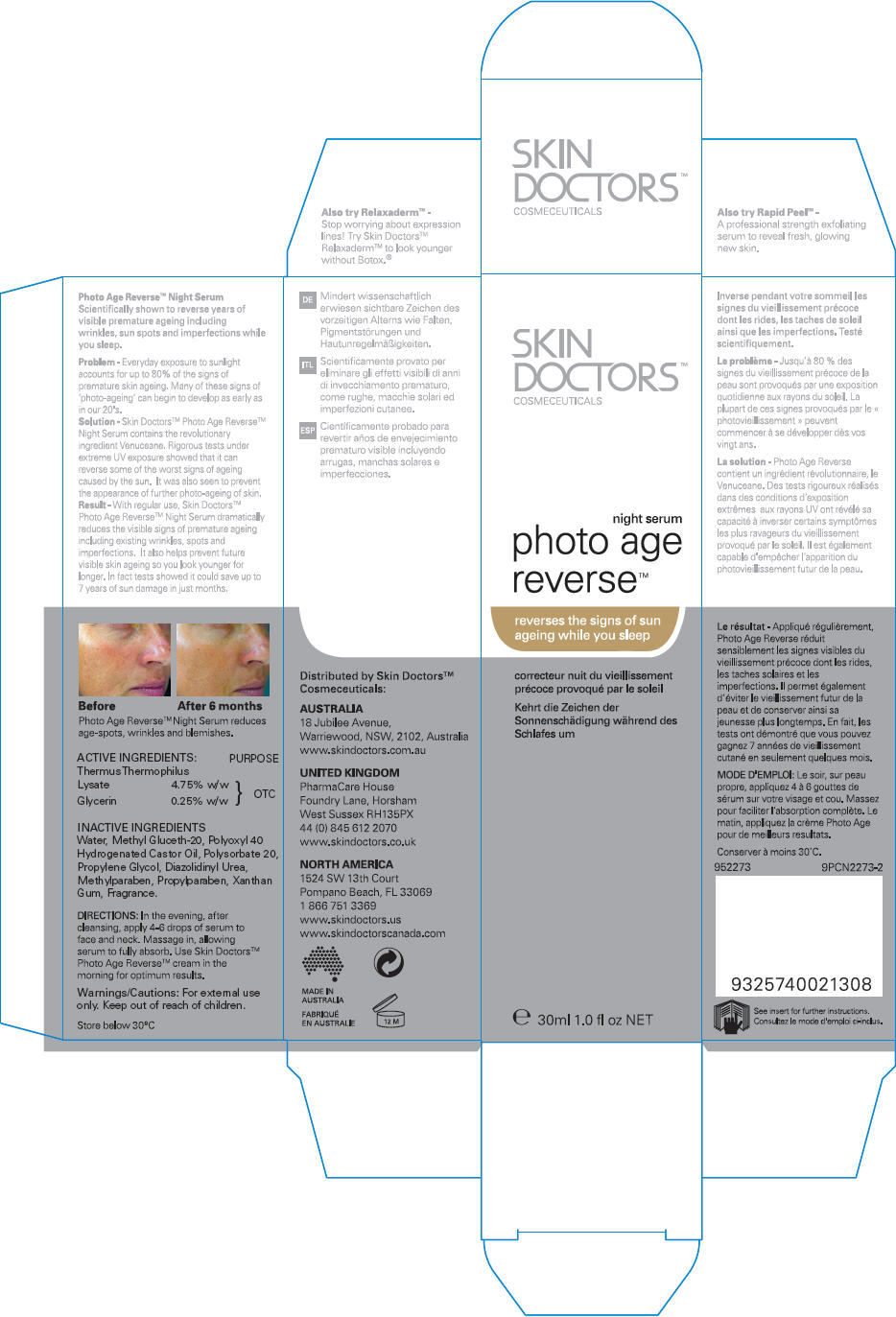 DRUG LABEL: Skin Doctors Photo Age Reverse Night Serum
NDC: 49203-730 | Form: LIQUID
Manufacturer: Cat Media Pty Ltd
Category: otc | Type: HUMAN OTC DRUG LABEL
Date: 20120712

ACTIVE INGREDIENTS: Thermus Thermophilus Lysate 48.2 mg/1 mL; Glycerin 2.54 mg/1 mL
INACTIVE INGREDIENTS: Water; Methyl Gluceth-20; Polyoxyl 40 Hydrogenated Castor Oil; Polysorbate 20; Propylene Glycol; Diazolidinyl Urea; Methylparaben; Propylparaben; Xanthan Gum; Phenoxyethanol; Potassium Sorbate

Skin Doctors™ Photo Age Reverse™ Night Serum

INDICATIONS AND USAGE

Scientifically shown to reverse years of visible premature ageing including wrinkles, sun spots and imperfections while you sleep.

Problem - Everyday exposure to sunlight accounts for up to 80% of the signs of premature skin ageing. Many of these signs of 'photo-ageing' can begin to develop as early as in our 20's.

Solution - Skin Doctors™ Photo Age Reverse™ Night Serum contains the revolutionary ingredient Venuceane. Rigorous tests under extreme UV exposure showed that it can reverse some of the worst signs of ageing caused by the sun. It was also seen to prevent the appearance of further photo-ageing of skin.

Result - With regular use, Skin Doctors™ Photo Age Reverse™ Night Serum dramatically reduces the visible signs of premature ageing including existing wrinkles, spots and imperfections. It also helps prevent future visible skin ageing so you look younger for longer. In fact tests showed it could save up to 7 years of sun damage in just months.

ACTIVE INGREDIENT

ACTIVE INGREDIENTS: |  | PURPOSE
Thermus Thermophilus Lysate | 4.75% w/w | OTC
Glycerin | 0.25% w/w | OTC

INACTIVE INGREDIENTS

Water, Methyl Gluceth-20, Polyoxyl 40 Hydrogenated Castor Oil, Polysorbate 20, Propylene Glycol, Diazolidinyl Urea, Methylparaben, Propylparaben, Xanthan Gum, Fragrance.

DIRECTIONS

In the evening, after cleansing, apply 4-6 drops of serum to face and neck. Massage in, allowing serum to fully absorb. Use Skin Doctors™ Photo Age Reverse™ cream in the morning for optimum results.

Warnings/Cautions

For external use only.

Keep out of reach of children.

STORAGE AND HANDLING

Store below 30°C

Distributed by Skin Doctors™
Cosmeceuticals:

NORTH AMERICA
1524 SW 13th Court
Pompano Beach, FL 33069

PRINCIPAL DISPLAY PANEL - 30 ml Bottle Carton

SKIN
DOCTORS™
COSMECEUTICALS

night serum
photo age
reverse™

reverses the signs of sun
ageing while you sleep

e 30ml 1.0 fl oz NET